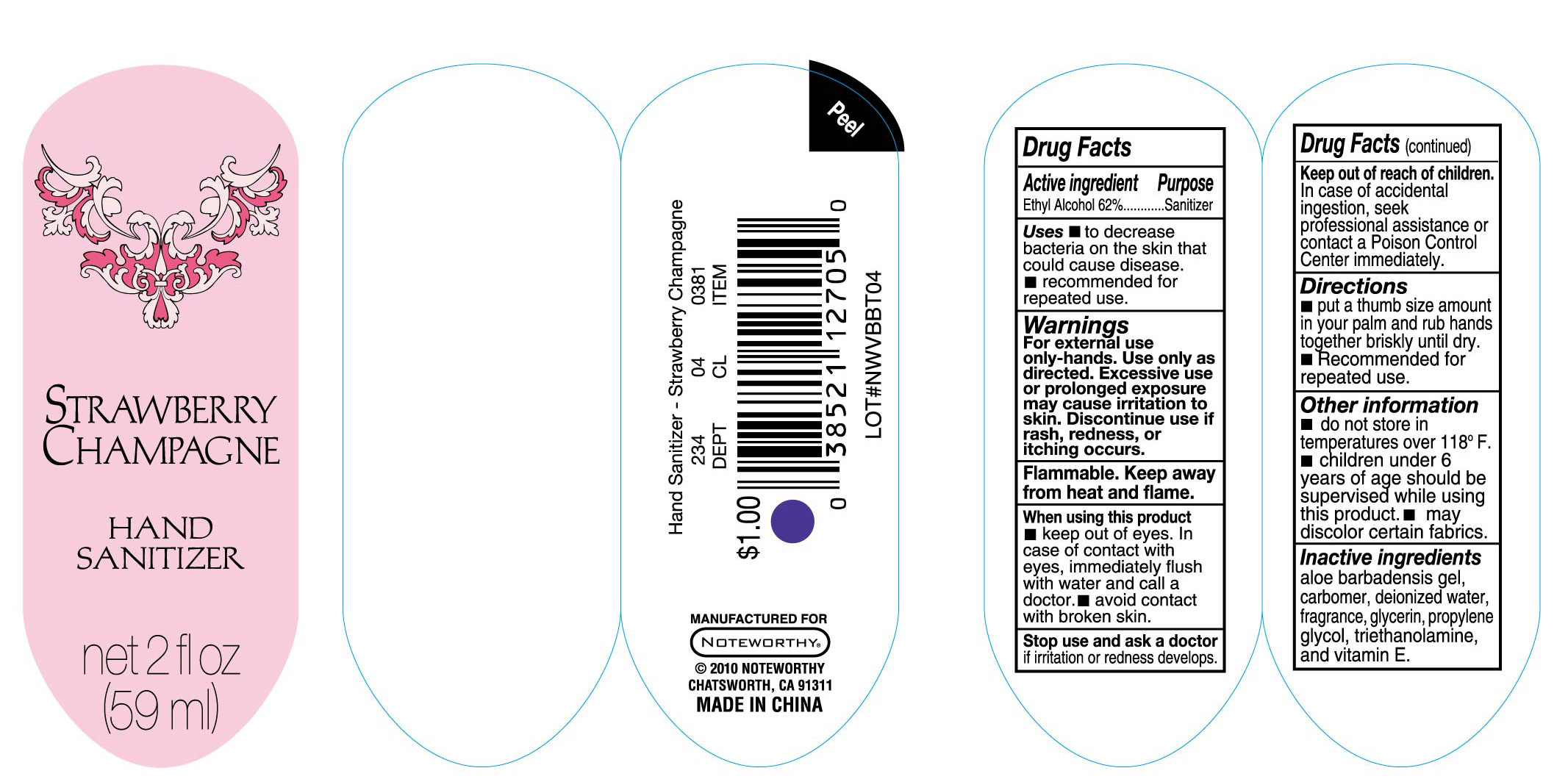 DRUG LABEL: Strawberry Champagne Hand Sanitizer
NDC: 25225-017 | Form: LIQUID
Manufacturer: Unique Holding Group Inc
Category: otc | Type: HUMAN OTC DRUG LABEL
Date: 20100703

ACTIVE INGREDIENTS: ALCOHOL 62 g/100 g
INACTIVE INGREDIENTS: Water 35.600 g/100 g; Propylene Glycol  0.5 g/100 g; Glycerin 1 g/100 g; ALOE VERA LEAF 0.01 g/100 g; CARBOMER HOMOPOLYMER TYPE C 0.33 g/100 g; ALPHA-TOCOPHEROL 0.01 g/100 g; TROLAMINE 0.35 g/100 g; STRAWBERRY 0.2 g/100 g

Drug Facts

Active Ingredient Purpose

Ethyl Alcohol 62% Sanitizer

Uses:

To decrease bacteria on the skin that could cause diseases

Recommended for repeated use

Warnings:

For external use only-hands. Use only as directed. Excessive use or prolonged exposure may cause irritation to skin. Discontinue use if rash, redness, or itching occurs.

Flammable. Keep away from heat and flame.

When using this product

- Keep out of eyes. In case of contacting with eyes, immediately flash with water and call a doctor.
- Avoid contacting with a broken skin.

STOP USE

Stop using and ask a doctor if irritation or redness develops.

Keep out of reach of children.

In case of accidental ingestion, seek professional assistance or contact a Poison Control Center immediately.

Directions

Put a thumb size amount in your palm and rub hands together briskly until dry.

Other Information

- Do not store in temperatures over 118F
- Children under six years of age should be supervise while using this product.
- May discolor certain fabrics.

Inactive Ingredients

aloe barbadensis gel, carbomer, deionized water, Fragrance, glycerin, propylene glycol, triethanolamine, and vitamin E

PACKAGE LABEL

lab